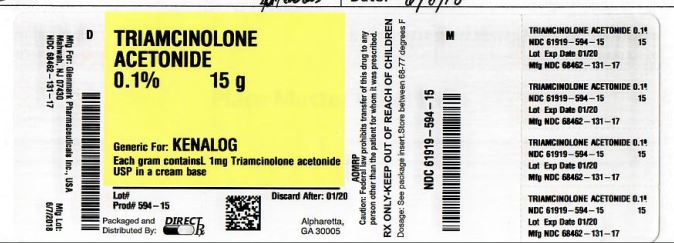 DRUG LABEL: TRIAMCINOLONE ACETONIDE
NDC: 61919-594 | Form: CREAM
Manufacturer: DIRECT RX
Category: prescription | Type: HUMAN PRESCRIPTION DRUG LABEL
Date: 20180807

ACTIVE INGREDIENTS: TRIAMCINOLONE ACETONIDE 1 mg/1 g
INACTIVE INGREDIENTS: MINERAL OIL; PROPYLENE GLYCOL; SORBITOL; POTASSIUM SORBATE; SORBIC ACID; WATER

TRIAMCINOLONE ACETONIDE 0.1% 30g

CONTRAINDICATIONS

Triamcinolone acetonide cream is contraindicated in those patients with a history of hypersensitivity to any of the components of the preparation.

OVERDOSAGE

Topically applied corticosteroids can be absorbed in sufficient amounts to produce systemic effects (See PRECAUTIONS).

DOSAGE AND ADMINISTRATION

Apply to the affected area as a thin film as follows: Triamcinolone Acetonide Cream USP, 0.025% two to four times daily; Triamcinolone Acetonide Cream USP, 0.1% and 0.5% two or three times daily depending on the severity of the condition. Occlusive dressings may be used for the management of psoriasis or recalcitrant conditions. If an infection develops, the use of occlusive dressings should be discontinued and appropriate antimicrobial therapy instituted.

HOW SUPPLIED

Triamcinolone Acetonide Cream USP, 0.025%

Triamcinolone Acetonide Cream USP, 0.1%

15 gram tubes NDC 0168-0003-15

15 gram tubes NDC 0168-0004-15

80 gram tubes NDC 0168-0003-80

80 gram tubes NDC 0168-0004-80

1 Lb jars NDC 0168-0004-16

Triamcinolone Acetonide Cream USP, 0.5%

15 gram tubes NDC 0168-0002-15.

Store at controlled room temperature 15°-30°C (59°-86°F).

Avoid excessive heat. Protect from freezing.

Fougera
PHARMACEUTICALS INC.

E. FOUGERA & CO.
A division of Fougera Pharmaceuticals Inc.
Melville New York 11747

I20215G/IF20215G
R09/11
#227

46165001A

R06/15

#65

ADVERSE REACTIONS

The following local adverse reactions are reported infrequently with topical corticosteroids, but may occur more frequently with the use of occlusive dressings. These reactions are listed in an approximate decreasing order of occurrence: burning, itching, irritation, dryness, folliculitis, hypertrichosis, acneiform eruptions, hypopigmentation, perioral dermatitis, allergic contact dermatitis, maceration of the skin, secondary infection, skin atrophy, striae and miliaria.

To report suspected adverse reactions1-888-463-6332

Rx only

DESCRIPTION

Triamcinolone Acetonide Cream USP contains Triamcinolone Acetonide [Pregna-1,4-diene-3,20-dione, 9-fluoro-11,21-dihydroxy-16,17-[(1-methylethylidene)bis- (oxy)]-, (11β,16α)-], with the empirical formula C24H31FO6 and molecular weight 434.50. CAS 76-25-5.

[chemstructure]

Triamcinolone Acetonide Cream USP, 0.025% contains: 0.25 mg of Triamcinolone Acetonide per gram in a base containing Emulsifying Wax, Cetyl Alcohol, Isopropyl Palmitate, Sorbitol Solution, Glycerin, Lactic Acid, Benzyl Alcohol and Purified Water.

Triamcinolone Acetonide Cream USP, 0.1% contains: 1 mg of Triamcinolone Acetonide per gram in a base containing Emulsifying Wax, Cetyl Alcohol, Isopropyl Palmitate, Sorbitol Solution, Glycerin, Lactic Acid, Benzyl Alcohol and Purified Water.

Triamcinolone Acetonide Cream USP, 0.5% contains: 5 mg of Triamcinolone Acetonide per gram in a base containing Emulsifying Wax, Cetyl Alcohol, Isopropyl Palmitate, Sorbitol Solution, Glycerin, Lactic Acid, Benzyl Alcohol and Purified Water.

Close
CLINICAL PHARMACOLOGY:
Topical corticosteroids share anti-inflammatory, anti-pruritic and vasoconstrictive actions. The mechanism of anti-inflammatory activity of the topical corticosteroids is unclear. Various ...
INDICATIONS AND USAGE:
Topical corticosteroids are indicated for the relief of the inflammatory and pruritic manifestations of corticosteroid-responsive dermatoses.
CONTRAINDICATIONS:(What is this?)
Topical corticosteroids are contraindicated in those patients with a history of hypersensitivity to any of the components of the preparation.
PRECAUTIONS:
General: Systemic absorption of topical corticosteroids has produced reversible hypothalamic-pituitary-adrenal (HPA) axis suppression, manifestations of Cushing's ...

CLINICAL PHARMACOLOGY

Topical corticosteroids share anti-inflammatory, anti-pruritic and vasoconstrictive actions. The mechanism of anti-inflammatory activity of the topical corticosteroids is unclear. Various laboratory methods, including vasoconstrictor assays, are used to compare and predict potencies and/or clinical efficacies of the topical corticosteroids. There is some evidence to suggest that a recognizable correlation exists between vasoconstrictor potency and therapeutic efficacy in man.

Pharmacokinetics: The extent of percutaneous absorption of topical corticosteroids is determined by many factors including the vehicle, the integrity of the epidermal barrier, and the use of occlusive dressings. Topical corticosteroids can be absorbed from normal intact skin. Inflammation and/or other disease processes in the skin increase percutaneous absorption. Occlusive dressings substantially increase the percutaneous absorption of topical corticosteroids. Thus, occlusive dressings may be a valuable therapeutic adjunct for treatment of resistant dermatoses (See DOSAGE AND ADMINISTRATION). Once absorbed through the skin, topical corticosteroids are handled through pharmacokinetic pathways similar to systemically administered corticosteroids. Corticosteroids are bound to plasma proteins in varying degrees. Corticosteroids are metabolized primarily in the liver and are then excreted by the kidneys. Some of the topical corticosteroids and their metabolites are also excreted into the bile.

INDICATIONS AND USAGE

Topical corticosteroids are indicated for the relief of the inflammatory and pruritic manifestations of corticosteroid-responsive dermatoses.